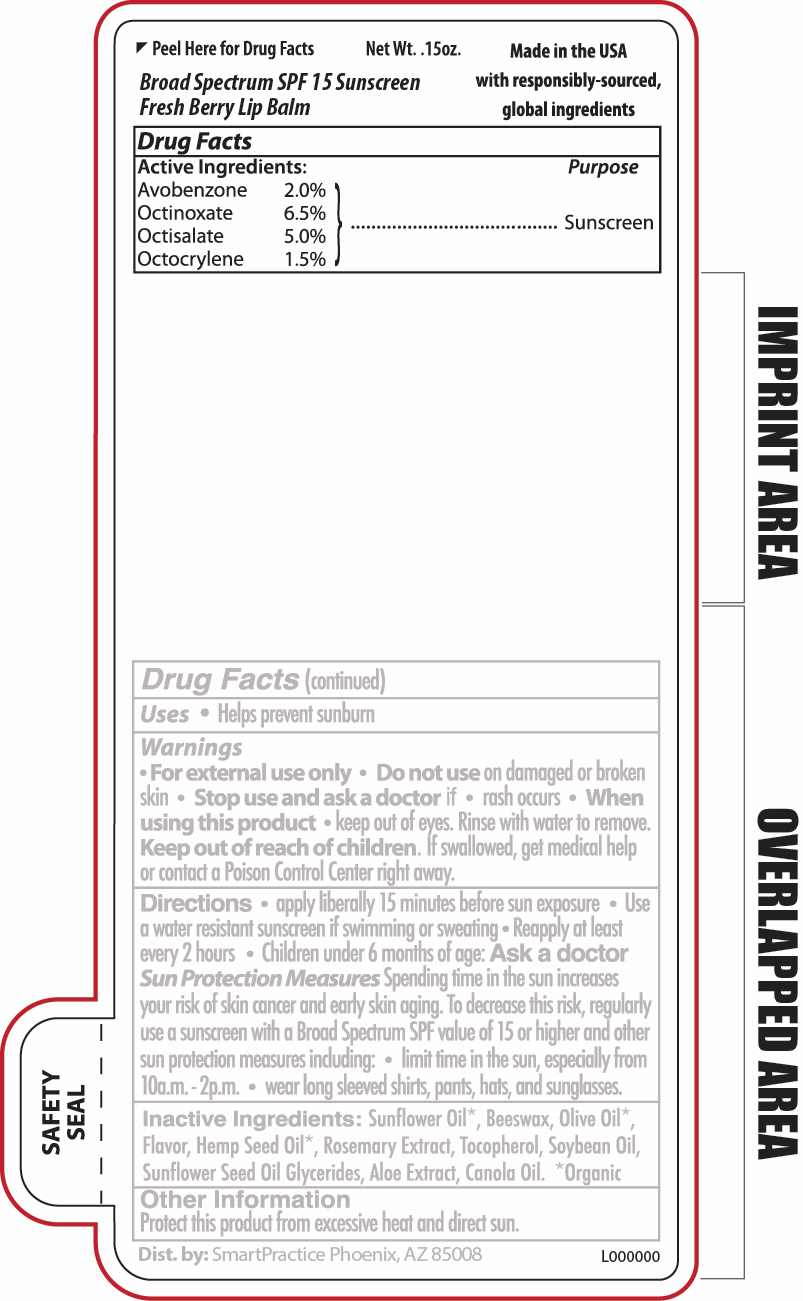 DRUG LABEL: Broad Spectrum SPF 15 Sunscreen Fresh Berry Lip Balm
NDC: 65692-0576 | Form: STICK
Manufacturer: Raining Rose, Inc
Category: otc | Type: HUMAN OTC DRUG LABEL
Date: 20240423

ACTIVE INGREDIENTS: OCTISALATE 0.21 g/4.25 g; OCTOCRYLENE 0.06 g/4.25 g; OCTINOXATE 0.28 g/4.25 g; AVOBENZONE 0.09 g/4.25 g
INACTIVE INGREDIENTS: TOCOPHEROL; SUNFLOWER OIL; CANNABIS SATIVA SEED OIL; CANOLA OIL; OLIVE OIL; ALOE VERA LEAF; SUNFLOWER OIL MONO/DIGLYCERIDES; WHITE WAX; ROSEMARY; SOYBEAN OIL

ACTIVE INGREDIENT

Avobenzone 2.0%

Octinoxate 6.5%

Octisalate 5.0%

Octocrylene 1.5%

PURPOSE

Sunscreen

WARNINGS

For external use only

DO NOT USE

on damaged or broken skin .

Stop use and ask a doctor if rash occurs

WHEN USING

Keep out of eyes. Rinse well with water to remove.

Keep out of reach of children.

If swallowed, get medical help or contact a Poison Control Center right away.

INACTIVE INGREDIENT

Sunflower Oil*, Beeswax, Olive Oil*, Flavor, Hemp Seed Oil*, Rosemary Extract, Tocopherol, Soybean Oil, Sunflower Seed Oil Glycerides, Aloe Extract, Canola Oil. * Organic

DOSAGE AND ADMINISTRATION

Apply liberally 15 mintues before sun exposure

INDICATIONS AND USAGE

Helps prevent sunburn